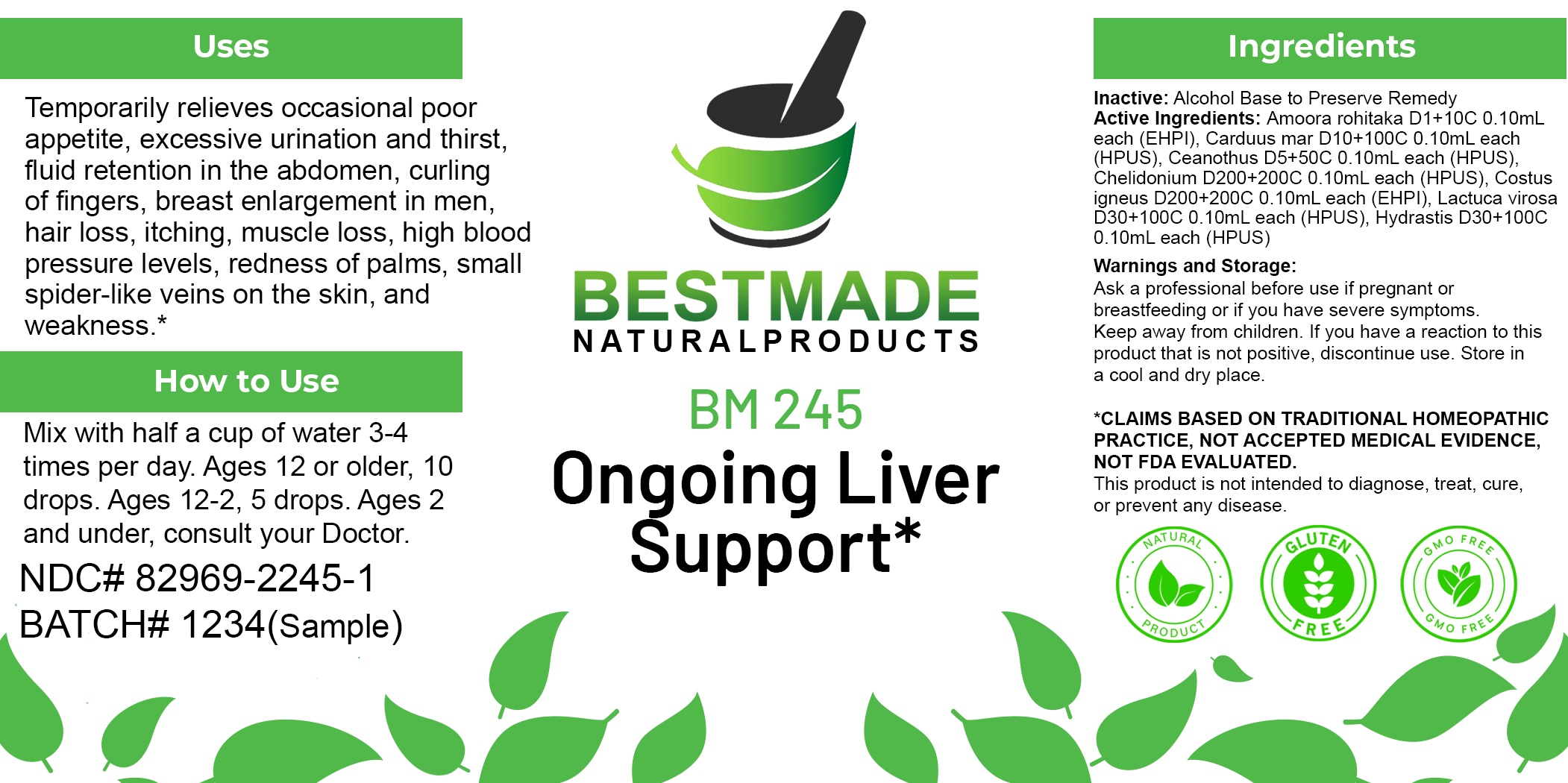 DRUG LABEL: Bestmade Natural Products BM245
NDC: 82969-2245 | Form: LIQUID
Manufacturer: Bestmade Natural Products
Category: homeopathic | Type: HUMAN OTC DRUG LABEL
Date: 20250304

ACTIVE INGREDIENTS: CHAMAECOSTUS CUSPIDATUS WHOLE 30 [hp_C]/30 [hp_C]; GOLDENSEAL 30 [hp_C]/30 [hp_C]; APHANAMIXIS POLYSTACHYA WHOLE 30 [hp_C]/30 [hp_C]; CHELIDONIUM MAJUS 30 [hp_C]/30 [hp_C]; CEANOTHUS AMERICANUS LEAF 30 [hp_C]/30 [hp_C]; LACTUCA VIROSA 30 [hp_C]/30 [hp_C]; MILK THISTLE 30 [hp_C]/30 [hp_C]
INACTIVE INGREDIENTS: ALCOHOL 30 [hp_C]/30 [hp_C]

BM245

DOSAGE AND ADMINISTRATION

How to Use

Mix with half a cup of water 3-4 times per day. Ages 12 or older, 10 drops. Ages 12-2, 5 drops. Ages 2 and under, consult your Doctor.

Inactive:

Alcohol Base to Preserve Product

ACTIVE INGREDIENT

Active Ingredients: Amoora rohitaka D1+10C 0.10mL each (EHPI), Carduus mar D10+100C 0.10mL each (HPUS), Ceanothus D5+50C 0.10mL each (HPUS), Chelidonium D200+200C 0.10mL each (HPUS), Costus igneus D200+200C 0.10mL each (EHPI), Lactuca virosa D30+100C 0.10mL each (HPUS), Hydrastis D30+100C 0.10mL each (HPUS)

KEEP OUT OF REACH OF CHILDREN

Warnings and Storage:

Ask a professional before use if pregnant or breastfeeding or if you have severe symptoms.

Keep away from children. If you have a reaction to this product that is not positive, discontinue use. Store in a cool and dry place

*CLAIMS BASED ON TRADITIONAL HOMEOPATHIC PRACTICE, NOT ACCEPTED MEDICAL EVIDENCE NOT FDA EVALUATED.
This product is not intended to diagnose, treat, cure, or prevent any disease.

Warnings and Storage:

Ask a professional before use if pregnant or breastfeeding or if you have severe symptoms.

Keep away from children. If you have a reaction to this product that is not positive, discontinue use. Store in a cool and dry place

*CLAIMS BASED ON TRADITIONAL HOMEOPATHIC PRACTICE, NOT ACCEPTED MEDICAL EVIDENCE NOT FDA EVALUATED.
This product is not intended to diagnose, treat, cure, or prevent any disease.

Uses
Temporarily relieves occasional poor appetite, excessive urination and thirst, fluid retention in the abdomen, curling of fingers, breast enlargement in men, hair loss, itching, muscle loss, high blood pressure levels, redness of palms, small spider-like veins on the skin, and weakness.*

Uses
Temporarily relieves occasional poor appetite, excessive urination and thirst, fluid retention in the abdomen, curling of fingers, breast enlargement in men, hair loss, itching, muscle loss, high blood pressure levels, redness of palms, small spider-like veins on the skin, and weakness.*

Entire package label